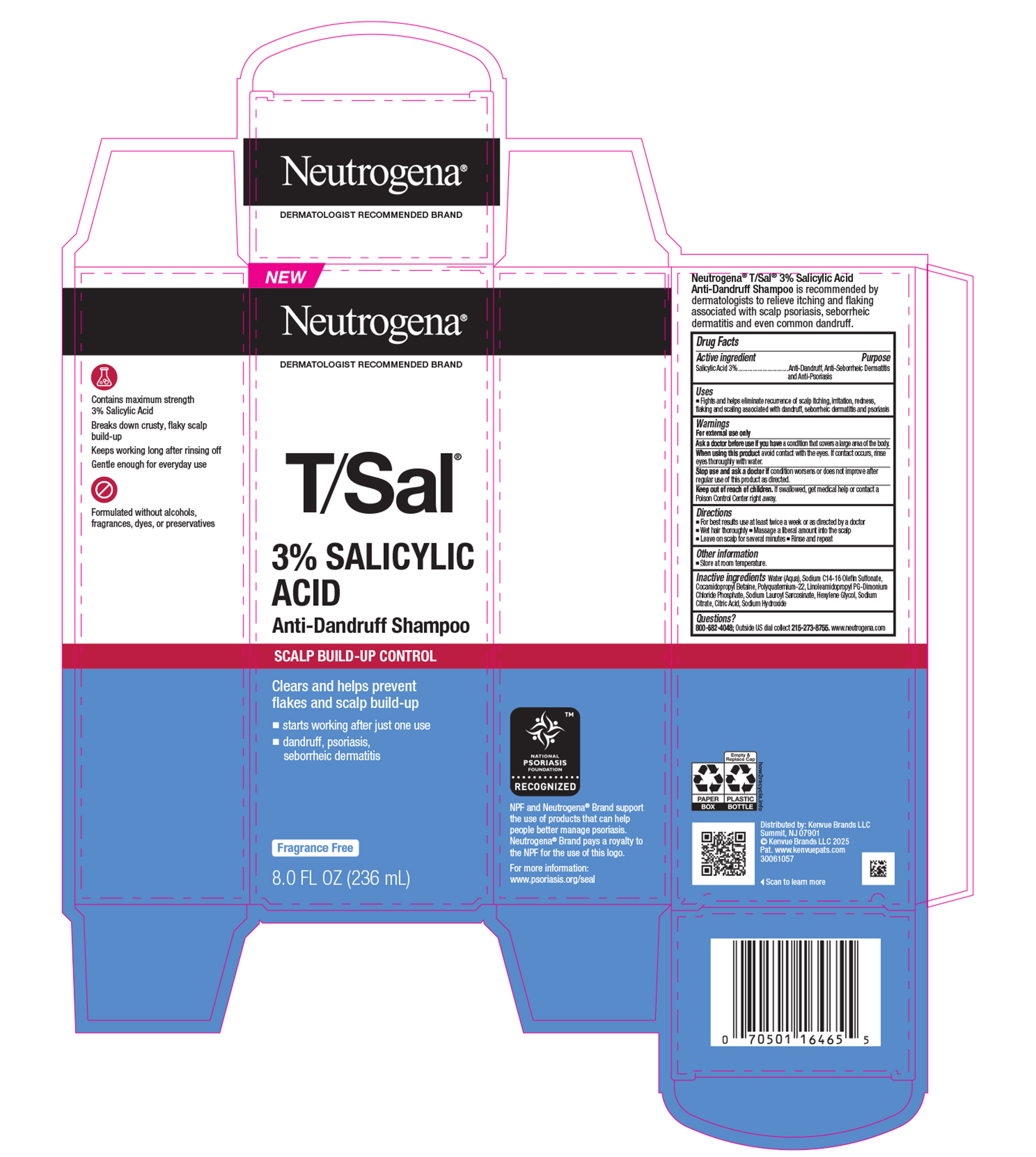 DRUG LABEL: NTG T/Sal 3% Salicylic Acid Anti-Dandruff for Scalp Build Up Control
NDC: 69968-0938 | Form: SHAMPOO
Manufacturer: Kenvue Brands LLC
Category: otc | Type: HUMAN OTC DRUG LABEL
Date: 20251222

ACTIVE INGREDIENTS: SALICYLIC ACID 30 mg/1 mL
INACTIVE INGREDIENTS: WATER; SODIUM C14-16 OLEFIN SULFONATE; COCAMIDOPROPYL BETAINE; SODIUM CITRATE; SODIUM LAUROYL SARCOSINATE; HEXYLENE GLYCOL; LINOLEAMIDOPROPYL PROPYLENE GLYCOL-DIMONIUM CHLORIDE PHOSPHATE; SODIUM HYDROXIDE; CITRIC ACID

NTG T/Sal 3% Salicylic Acid Anti-Dandruff Shampoo for Scalp Build Up Control

Drug Facts

Active ingredient

Salicylic Acid (3%)

Purposes

Anti-Dandruff, Anti-Seborrheic Dermatitis and Anti-Psoriasis

Use

Fights and helps eliminate recurrence of scalp itching, irritation, redness, flaking and scaling associated with dandruff, seborrheic dermatitis and psoriasis

Warnings

For external use only.

Ask a doctor before use if you have a condition that covers a large area of the body.

When using this product avoid contact with the eyes. If contact occurs, rinse eyes thoroughly with water.

Stop use and ask a doctor if condition worsens or does not improve after regular use of this product as directed.

Keep out of reach of children. If swallowed, get medical help or contact a Poison Control Center right away.

Directions

For best results use at least twice a week or as directed by a doctor

- Wet hair thoroughly
- Massage a liberal amount into the scalp
- Leave on scalp for several minutes
- Rinse and repeat

Other information

Store at room temperature.

Inactive ingredients

Water (Aqua), Sodium C14-16 Olefin Sulfonate, Cocamidopropyl Betaine, Polyquaternium-22, Linoleamidopropyl PG-Dimonium Chloride Phosphate, Sodium Lauroyl Sarcosinate, Hexylene Glycol, Sodium Citrate, Citric Acid, Sodium Hydroxide

Questions?

800-582-4048; Outside US dial collect 215-273-8755. www.neutrogena.com

Distributed by:
Kenvue Brands LLC
Summit, NJ 07901

PRINCIPAL DISPLAY PANEL - 236 mL Bottle in a Carton

NEW

Neutrogena®

DERMATOLOGIST RECOMMENDED BRAND

T/Sal®

3% SALICYLIC

ACID

Anti-Dandruff Shampoo

SCALP BUILD-UP CONTROL

Clears and helps prevent

flakes and scalp build-up

- starts working after just one use
- dandruff, psoriasis,
- seborrheic dermatitis

Fragrance Free

8.0 FL OZ (236 mL)